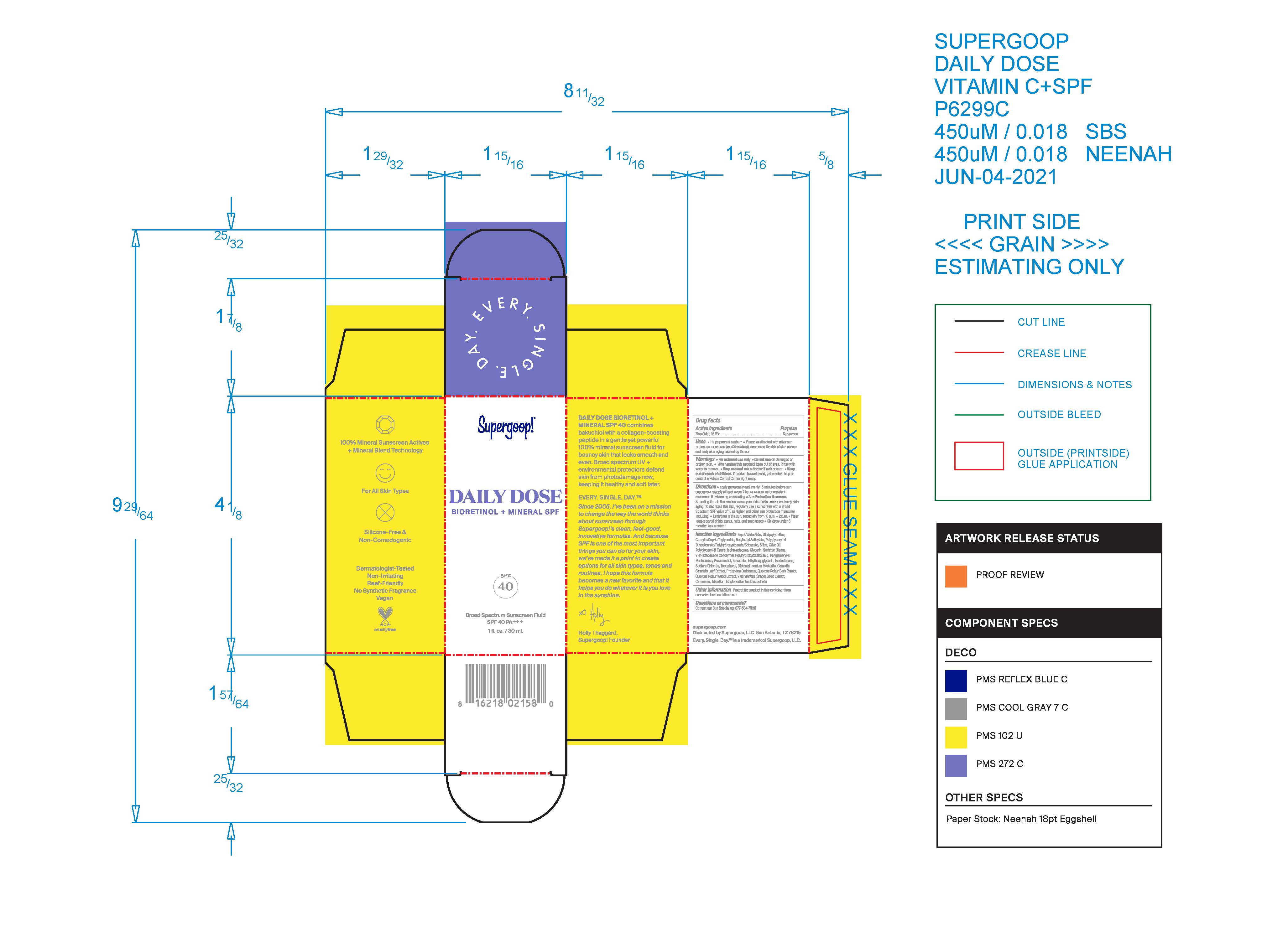 DRUG LABEL: Daily Dose Bioretinol Mineral SPF 40
NDC: 75936-604 | Form: LIQUID
Manufacturer: Supergoop, LLC
Category: otc | Type: HUMAN OTC DRUG LABEL
Date: 20241205

ACTIVE INGREDIENTS: ZINC OXIDE 16.5 g/100 mL
INACTIVE INGREDIENTS: QUERCUS ROBUR TWIG BARK; DICAPRYLYL ETHER; BUTYLOCTYL SALICYLATE; POLYGLYCERYL-4 DIISOSTEARATE/POLYHYDROXYSTEARATE/SEBACATE; SODIUM CHLORIDE; TOCOPHEROL; CAMELLIA SINENSIS FLOWER; PROPYLENE CARBONATE; QUERCUS ROBUR WOOD; WATER; MEDIUM-CHAIN TRIGLYCERIDES; SILICON DIOXIDE; OLIVE OIL POLYGLYCERYL-6 ESTERS; POLYHYDROXYSTEARIC ACID (2300 MW); ISOHEXADECANE; GLYCERIN; POLYGLYCERYL-6 DIOLEATE; PEG-6 SORBITAN OLEATE; VINYLPYRROLIDONE/HEXADECENE COPOLYMER; ETHYLHEXYLGLYCERIN; VITIS VINIFERA SEED; TRISODIUM ETHYLENEDIAMINE DISUCCINATE; PROPANEDIOL; BAKUCHIOL; ISODODECANE; DISTEARDIMONIUM HECTORITE; CARNOSINE

Daily Dose Bioretinol + Mineral SPF 40

ACTIVE INGREDIENT

Zinc Oxide 16.5% Sunscreen

Uses

Helps prevent sunburn

If used as directed with other sun protection measures (see Directions), decreases the risk of Skin cancer and early skin aging caused by the sun

KEEP OUT OF REACH OF CHILDREN

Keep our of reach of children. If product is swallowed, get medical help or contact a Poison Control Center right away

Stop use and ask a doctor if rash occurs.

WARNINGS

For External use only

Do not use on damaged or broken skin

When using this product, Keep our of eyes. Rinse with water to remove

Directions

• apply generously and evenly 15 minutes before sun exposure
• reapply at least every 2 hours
• use a water resistant sunscreen if swimming or sweating

Sun Protection Measures: Spending time in the sun increases your risk of skin cancer and early skin aging. To decrease this risk, regularly use a sunscreen with a Broad Spectrum SPF value of 15 or higher and other sun protection measures including: ◦ Limit time in the sun, especially from 10 a.m. - 2 p.m. ◦ Wear long-sleeved shirts, pants, hats, and sunglasses • Children under 6 months: Ask a doctor

Inactive Ingredients:

Aqua/Water/Eau, Dicaprylyl Ether, Caprylic/Capric Triglyceride, Butyloctyl Salicylate, Polyglyceryl-4 Diisostearate/Polyhydroxystearate/Sebacate, Silica, Olive Oil Polyglyceryl-6 Esters, Isohexadecane, Glycerin, Sorbitan Oleate, VP/Hexadecene Copolymer, Polyhydroxystearic acid, Polyglyceryl-6 Pentaoleate, Propanediol, Bakuchiol, Ethylhexylglycerin, Isododecane, Sodium Chloride, Tocopherol, Disteardimonium Hectorite, Camellia Sinensis Leaf Extract, Propylene Carbonate, Quercus Robur Bark Extract, Quercus Robur Wood Extract, Vitis Vinifera (Grape) Seed Extract, Carnosine, Trisodium Ethylenediamine Disuccinate

PACKAGE LABEL

Daily Dose Bioretinol + Mineral SPF

SPF 40

Broad Spectrum Sunscreen Fluid

1 fl. oz. / 30 mL